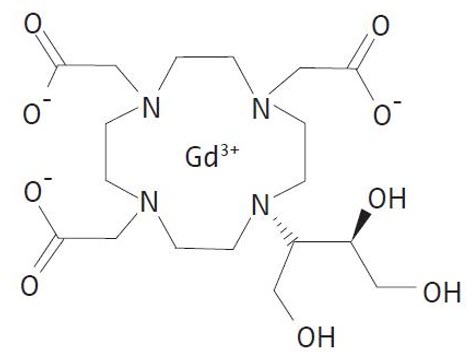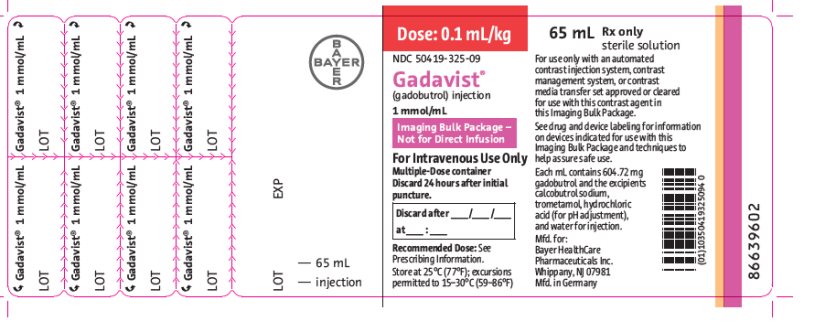 DRUG LABEL: Gadavist
NDC: 50419-325 | Form: INJECTION
Manufacturer: Bayer HealthCare Pharmaceuticals Inc.
Category: prescription | Type: HUMAN PRESCRIPTION DRUG LABEL
Date: 20260227

ACTIVE INGREDIENTS: GADOBUTROL 604.72 mg/1 mL
INACTIVE INGREDIENTS: TROMETHAMINE; HYDROCHLORIC ACID; WATER

HIGHLIGHTS OF PRESCRIBING INFORMATION

These highlights do not include all the information needed to use GADAVIST safely and effectively. See full prescribing information for GADAVIST.
GADAVIST (gadobutrol) injection, for intravenous use
Initial U.S. Approval: 2011

WARNING: RISK ASSOCIATED WITH INTRATHECAL USE and NEPHROGENIC SYSTEMIC FIBROSIS

See full prescribing information for complete boxed warning.

- Intrathecal administration of gadolinium-based contrast agents (GBCAs) can cause serious adverse reactions including death, coma, encephalopathy, and seizures. GADAVIST is not approved for intrathecal use. (5.1)
- GBCAs increase the risk for nephrogenic systemic fibrosis (NSF) among patients with impaired elimination of the drugs. Avoid use of GADAVIST in these patients unless the diagnostic information is essential and not available with non-contrasted MRI or other modalities.
  The risk for NSF appears highest among patients with:
  - Chronic, severe kidney disease (GFR < 30 mL/min/1.73m^2), or
  - Acute kidney injury.
  Screen patients for acute kidney injury and other conditions that may reduce renal function. For patients at risk for chronically reduced renal function (for example, age >60 years, hypertension or diabetes), estimate the glomerular filtration rate (GFR) through laboratory testing. (5.2)

RECENT MAJOR CHANGES

Warnings and Precautions, Acute Respiratory Distress Syndrome (5.4) | 3/2025

1 INDICATIONS AND USAGE

GADAVIST is a gadolinium-based contrast agent indicated for use with magnetic resonance imaging (MRI):

- To detect and visualize areas with disrupted blood brain barrier and/or abnormal vascularity of the central nervous system in adult and pediatric patients including term neonates
- To assess the presence and extent of malignant breast disease in adult patients
- To evaluate known or suspected supra-aortic or renal artery disease in adult and pediatric patients including term neonates
- To assess myocardial perfusion (stress, rest) and late gadolinium enhancement in adult patients with known or suspected coronary artery disease (CAD) (1)

2 DOSAGE AND ADMINISTRATION

- Recommended dose for adults and pediatric patients, including term neonates, is 0.1 mmol/kg actual body weight (equivalent to 0.1 mL/kg) administered by intravenous bolus injection. (2.1, 2.2)
- See Full Prescribing Information for administration, imaging, and handling. (2.2, 2.3)

3 DOSAGE FORMS AND STRENGTHS

Injection: 1 mmol/mL of gadobutrol available in single-dose vial, single-dose prefilled syringe, and imaging bulk package (3)

4 CONTRAINDICATIONS

History of severe hypersensitivity reaction to GADAVIST (4)

5 WARNINGS AND PRECAUTIONS

- Hypersensitivity Reactions: Anaphylactic and other hypersensitivity reactions with cardiovascular, respiratory or cutaneous manifestations, ranging from mild to severe, including death, have occurred. Monitor patients closely during and after administration of GADAVIST. (5.3)
- Acute Respiratory Distress Syndrome: For patients demonstrating respiratory distress after administration, assess oxygen requirement and monitor for worsening respiratory function. (5.4)
- Gadolinium Retention: Gadolinium is retained for months or years in brain, bone, and other organs. (5.5)

6 ADVERSE REACTIONS

Most common adverse reactions (incidence ≥ 0.5%) are headache, nausea, and dizziness. (6.1)

To report SUSPECTED ADVERSE REACTIONS, contact Bayer HealthCare Pharmaceuticals Inc. at 1-888-842-2937 or FDA at 1-800-FDA-1088 or www.fda.gov/medwatch

8 USE IN SPECIFIC POPULATIONS

Pregnancy: Use only if imaging is essential during pregnancy and cannot be delayed. (8.1)

FULL PRESCRIBING INFORMATION

WARNING: RISK ASSOCIATED WITH INTRATHECAL USE and NEPHROGENIC SYSTEMIC FIBROSIS

Risk Associated with Intrathecal Use

Intrathecal administration of gadolinium-based contrast agents (GBCAs) can cause serious adverse reactions including death, coma, encephalopathy, and seizures. GADAVIST is not approved for intrathecal use [see Warnings and Precautions (5.1)].

Nephrogenic Systemic Fibrosis

GBCAs increase the risk for nephrogenic systemic fibrosis (NSF) among patients with impaired elimination of the drugs. Avoid use of GADAVIST in these patients unless the diagnostic information is essential and not available with non-contrasted MRI or other modalities. NSF may result in fatal or debilitating fibrosis affecting the skin, muscle and internal organs.

The risk for NSF appears highest among patients with:

- Chronic, severe kidney disease (GFR < 30 mL/min/1.73m^2), or
- Acute kidney injury.

Screen patients for acute kidney injury and other conditions that may reduce renal function. For patients at risk for chronically reduced renal function (for example, age > 60 years, hypertension or diabetes), estimate the glomerular filtration rate (GFR) through laboratory testing.

For patients at highest risk for NSF, do not exceed the recommended GADAVIST dose and allow a sufficient period of time for elimination of the drug from the body prior to any re-administration [see Warnings and Precautions (5.2)].

1 INDICATIONS AND USAGE

GADAVIST is indicated for:

- Magnetic resonance imaging (MRI) of the central nervous system (CNS) to detect and visualize areas with disrupted blood brain barrier and/or abnormal vascularity in adult and pediatric patients including term neonates
- MRI of the breast to assess the presence and extent of malignant breast disease in adult patients
- Magnetic resonance angiography (MRA) to evaluate known or suspected supra-aortic or renal artery disease in adult and pediatric patients including term neonates
- Cardiac MRI (CMRI) to assess myocardial perfusion (stress, rest) and late gadolinium enhancement in adult patients with known or suspected coronary artery disease (CAD)

2 DOSAGE AND ADMINISTRATION

2.1 Recommended Dose

The recommended dose of GADAVIST for adult and pediatric patients, including term neonates, is 0.1 mmol/kg actual body weight (equivalent to 0.1 mL/kg) administered intravenously.

For CMRI, the dose is divided into two separate, equal injections [see Dosage and Administration (2.2)].

Refer to Table 1 for volumes to be administered for example body weights.

Table 1: Volume of GADAVIST for Example Body Weights
Body Weight (kg) | Volume to be Administered (mL)
2.5 | 0.25
5 | 0.5
10 | 1
15 | 1.5
20 | 2
25 | 2.5
30 | 3
35 | 3.5
40 | 4
45 | 4.5
50 | 5
60 | 6
70 | 7
80 | 8
90 | 9
100 | 10
110 | 11
120 | 12
130 | 13
140 | 14

2.2 Administration and Imaging Instructions

General

- GADAVIST is formulated at a higher concentration (1 mmol/mL) compared to certain other gadolinium-based contrast agents, resulting in a lower volume of administration [see Dosage and Administration (2.1)].
- GADAVIST is for intravenous use only and must not be administered intrathecally [see Warnings and Precautions (5.1)].
- Use aseptic technique when preparing and administering GADAVIST.
- Visually inspect GADAVIST for particulate matter and discoloration prior to administration. Do not use the solution if it is discolored, if particulate matter is present, or if the container appears damaged.
- If solidification occurs due to cold exposure, bring GADAVIST to room temperature before use and inspect to ensure that the solution is clear and colorless to pale yellow.
- Do not mix GADAVIST with other medications and do not administer GADAVIST in the same intravenous line simultaneously with other medications.

MRI of the CNS in Adult and Pediatric Patients Including Term Neonates

- Administer GADAVIST as an intravenous injection, manually or by power injector, at a flow rate of approximately 2 mL/sec.
- Follow GADAVIST injection with a flush of 0.9% Sodium Chloride Injection to ensure complete administration of the contrast.
- Post contrast MRI can commence immediately following contrast administration.

MRI of the Breast in Adults

- Administer GADAVIST as an intravenous bolus by power injector, followed by a flush of 0.9% Sodium Chloride Injection to ensure complete administration of the contrast.
- Start image acquisition following GADAVIST administration and then repeat sequentially to determine peak intensity and wash-out.

MR Angiography in Adult and Pediatric Patients Including Term Neonates

- Image acquisition should coincide with peak arterial concentration, which varies among patients.
- For adults, administer GADAVIST as an intravenous injection by power injector, at a flow rate of approximately 1.5 mL/sec, followed by a 30 mL flush of 0.9% Sodium Chloride Injection at the same rate to ensure complete administration of the contrast.
- For pediatric patients including term neonates, administer GADAVIST as an intravenous injection by power injector or manually, followed by a flush of 0.9% Sodium Chloride Injection to ensure complete administration of the contrast.

Cardiac MRI in Adults

- Administer GADAVIST through a separate intravenous line in the contralateral arm if concomitantly providing a continuous infusion of a pharmacologic stress agent.
- Administer GADAVIST as two separate bolus injections: 0.05 mmol/kg actual body weight (equivalent to 0.05 mL/kg) at peak pharmacologic stress followed by 0.05 mmol/kg (equivalent to 0.05 mL/kg) at rest.
- Administer GADAVIST via a power injector at a flow rate of approximately 4 mL/sec and follow each injection with a 20 mL flush of 0.9% Sodium Chloride Injection at the same flow rate.

2.3 Directions for Use of Single-Dose Containers

Single-Dose Vials

- Draw GADAVIST into the syringe immediately before use.
- Pierce the rubber stopper only once.
- Discard any unused vial contents.

Single-Dose Prefilled Syringes

- Remove the tip cap from the prefilled syringe immediately before use.
- Discard any unused syringe contents.

2.4 Directions for Use of Imaging Bulk Package

- GADAVIST Imaging Bulk Package (IBP) contains many single doses for use only with an automated contrast injection system, contrast management system, or contrast media transfer set approved or cleared for use with this contrast agent in this IBP.
- See drug and device labeling for information on devices indicated for use with this IBP and techniques to help assure safe use.
- The IBP is to be used only in a room designated for radiological procedures that involve intravascular administration of a contrast agent.
- Utilize aseptic technique for penetrating the container closure of the IBP and transferring GADAVIST.
- Penetrate the container closure only one time with a suitable sterile component of the automated contrast injection system, contrast management system, or contrast media transfer set (e.g., transfer spike) approved or cleared for use with this contrast agent in this IBP.
- Once the IBP is punctured, do not remove it from the work area during the entire period of use. Storage temperature of GADAVIST IBP after the closure has been entered is 20°C to 25°C (68°F to 77°F).
- Maximum use time from puncture is 24 hours. Discard any unused portion 24 hours after puncture of the IBP.
- After the container closure is punctured, if the integrity of the IBP and the delivery system cannot be assured through direct continuous supervision, the IBP and all associated disposable components for the automated contrast injection system, contrast management system, or contrast media transfer set (e.g., transfer spike) should be discarded.

3 DOSAGE FORMS AND STRENGTHS

Injection: 1 mmol/mL of gadobutrol as a clear and colorless to pale yellow solution available in the following strengths:

Strength | Package Type
- 2 mmol/2 mL (1 mmol/mL) - 7.5 mmol/7.5 mL (1 mmol/mL) - 10 mmol/10 mL (1 mmol/mL) - 15 mmol/15 mL (1 mmol/mL) | Single-Dose Vial
- 7.5 mmol/7.5 mL (1 mmol/mL) - 10 mmol/10 mL (1 mmol/mL) - 15 mmol/15 mL (1 mmol/mL) | Single-Dose Prefilled Syringe
- 30 mmol/30 mL (1 mmol/mL) - 65 mmol/65 mL (1 mmol/mL) | Imaging Bulk Package

4 CONTRAINDICATIONS

GADAVIST is contraindicated in patients with history of severe hypersensitivity reactions to GADAVIST [see Warnings and Precautions (5.3)].

5 WARNINGS AND PRECAUTIONS

5.1 Risk Associated with Intrathecal Use

Intrathecal administration of GBCAs can cause serious adverse reactions including death, coma, encephalopathy, and seizures. The safety and effectiveness of GADAVIST have not been established with intrathecal use. GADAVIST is not approved for intrathecal use [see Dosage and Administration (2.2)].

5.2 Nephrogenic Systemic Fibrosis

GBCAs increase the risk for nephrogenic systemic fibrosis (NSF) among patients with impaired elimination of the drugs. Avoid use of GADAVIST among these patients unless the diagnostic information is essential and not available with non-contrast MRI or other modalities. The GBCA-associated NSF risk appears highest for patients with chronic, severe kidney disease (GFR < 30 mL/min/1.73m^2) as well as patients with acute kidney injury. The risk appears lower for patients with chronic, moderate kidney disease (GFR 30 to 59 mL/min/1.73m^2) and little, if any, for patients with chronic, mild kidney disease (GFR 60 to 89 mL/min/1.73m^2). NSF may result in fatal or debilitating fibrosis affecting the skin, muscle and internal organs. Report any diagnosis of NSF following GADAVIST administration to Bayer Healthcare (1-888-842-2937) or FDA (1-800-FDA-1088 or www.fda.gov/medwatch).

Screen patients for acute kidney injury and other conditions that may reduce renal function. Features of acute kidney injury consist of rapid (over hours to days) and usually reversible decrease in kidney function, commonly in the setting of surgery, severe infection, injury or drug-induced kidney toxicity. Serum creatinine levels and estimated GFR may not reliably assess renal function in the setting of acute kidney injury. For patients at risk for chronically reduced renal function (for example, age > 60 years, diabetes mellitus or chronic hypertension), estimate the GFR through laboratory testing.

Among the factors that may increase the risk for NSF are repeated or higher than recommended doses of a GBCA and degree of renal impairment at the time of exposure. Record the specific GBCA and the dose administered to a patient. For patients at highest risk for NSF, do not exceed the recommended GADAVIST dose and allow a sufficient period of time for elimination of the drug prior to re-administration. For patients receiving hemodialysis, consider the prompt initiation of hemodialysis following the administration of a GBCA in order to enhance the contrast agent's elimination [see Use in Specific Populations (8.6) and Clinical Pharmacology (12.3)]. The usefulness of hemodialysis in the prevention of NSF is unknown.

5.3 Hypersensitivity Reactions

Anaphylactic and other hypersensitivity reactions with cardiovascular, respiratory or cutaneous manifestations, ranging from mild to severe, have occurred following GADAVIST administration [see Adverse Reactions (6.1, 6.2)]. There have been reports of life-threatening and fatal outcomes from these adverse reactions. Most hypersensitivity reactions to GADAVIST have occurred within half an hour after administration. Delayed reactions can occur up to several days after administration.

- Before GADAVIST administration, assess all patients for any history of a reaction to contrast media, bronchial asthma and/or allergic disorders. These patients may have an increased risk for a hypersensitivity reaction to GADAVIST.
- GADAVIST is contraindicated in patients with history of hypersensitivity reactions to GADAVIST [see Contraindications (4)].
- Administer GADAVIST only in situations where trained personnel and therapies are promptly available for the treatment of hypersensitivity reactions, including personnel trained in resuscitation.
- Observe patients for signs and symptoms of hypersensitivity reactions during and following GADAVIST administration.

5.4 Acute Respiratory Distress Syndrome

Acute respiratory distress syndrome (ARDS) has been reported in patients administered GADAVIST and may be characterized by severe hypoxemia requiring oxygen support and mechanical ventilation. These manifestations may resemble an immediate hypersensitivity reaction with onset of respiratory distress within <30 minutes to 24 hours after GADAVIST administration. For patients demonstrating respiratory distress after GADAVIST administration, assess oxygen requirement and monitor for worsening respiratory function.

5.5 Gadolinium Retention

Gadolinium is retained for months or years in several organs. The highest concentrations (nanomoles per gram of tissue) have been identified in the bone, followed by other organs (for example, brain, skin, kidney, liver, and spleen). The duration of retention also varies by tissue and is longest in bone. Linear GBCAs cause more retention than macrocyclic GBCAs. At equivalent doses, gadolinium retention varies among the linear agents with gadodiamide causing greater retention than other linear agents such as gadoxetate disodium and gadobenate dimeglumine. Retention is lowest and similar among the macrocyclic GBCAs such as gadoterate meglumine, gadobutrol, gadoteridol, and gadopiclenol.

Consequences of gadolinium retention in the brain have not been established. Pathologic and clinical consequences of GBCA administration and retention in skin and other organs have been established in patients with impaired renal function [see Warnings and Precautions (5.2)]. There are rare reports of pathologic skin changes in patients with normal renal function. Adverse events involving multiple organ systems have been reported in patients with normal renal function without an established causal link to gadolinium retention [see Adverse Reactions (6.2)].

While clinical consequences of gadolinium retention have not been established in patients with normal renal function, certain patients might be at higher risk. These include patients requiring multiple lifetime doses, pregnant and pediatric patients, and patients with inflammatory conditions. Consider the retention characteristics of the agent when choosing a GBCA for these patients. Minimize repetitive GBCA imaging studies particularly closely spaced studies, when possible.

5.6 Acute Kidney Injury

In patients with chronic renal impairment, acute kidney injury sometimes requiring dialysis has been observed with the use of some GBCAs. Do not exceed the recommended dose; the risk of acute kidney injury may increase with higher than recommended doses.

5.7 Extravasation and Injection Site Reactions

Injection site reactions have been reported in clinical studies with GADAVIST [see Adverse Reactions (6.1)]. Extravasation into tissues during GADAVIST administration may result in moderate irritation [see Nonclinical Toxicology (13.2)]. Ensure catheter and venous patency before the injection of GADAVIST.

5.8 Overestimation of Extent of Malignant Disease in MRI of the Breast

GADAVIST MRI of the breast overestimated the histologically confirmed extent of malignancy in the diseased breast in up to 50% of the patients [see Clinical Studies (14.2)].

5.9 Low Sensitivity for Significant Arterial Stenosis

The performance of GADAVIST MRA for detecting arterial segments with significant stenosis (>50% renal, >70% supra-aortic) has not been shown to exceed 55%. Therefore, a negative MRA study alone should not be used to rule out significant stenosis [see Clinical Studies (14.3)].

6 ADVERSE REACTIONS

The following clinically significant adverse reactions are discussed elsewhere in labeling:

- Nephrogenic Systemic Fibrosis [see Warnings and Precautions (5.2)]
- Hypersensitivity Reactions [see Contraindications (4) and Warnings and Precautions (5.3)]
- Acute Respiratory Distress Syndrome [see Warnings and Precautions (5.4)]

6.1 Clinical Trials Experience

Because clinical trials are conducted under widely varying conditions, adverse reaction rates observed in the clinical trials of a drug cannot be directly compared to rates in the clinical trials of another drug and may not reflect the rates observed in clinical practice.

The safety of GADAVIST was evaluated in 7,713 subjects (including 184 pediatric population, ages 0 to 17 years) who received GADAVIST in clinical trials. Approximately 52% of the subjects were male and the racial and ethnic distribution was 62% White, 28% Asian, 5% Hispanic or Latino, 2.5% Black or African American, and 2.5% other ethnic groups. The average age was 56 years (range from 1 week to 93 years).

Table 2 lists adverse reactions that occurred in ≥ 0.1% subjects who received GADAVIST.

Table 2: Adverse Reactions Reported in ≥0.1% Subjects who Received GADAVIST in Clinical Trials
Adverse Reaction | GADAVIST n=7,713 Rate (%)
Headache | 1.7
Nausea | 1.2
Dizziness | 0.5
Dysgeusia | 0.4
Feeling Hot | 0.4
Injection site reactions | 0.4
Vomiting | 0.4
Rash (includes generalized, macular, papular, pruritic) | 0.3
Erythema | 0.2
Paresthesia | 0.2
Pruritus (includes generalized) | 0.2
Dyspnea | 0.1
Urticaria | 0.1

Adverse reactions that occurred with a frequency of < 0.1% in subjects who received GADAVIST include: hypersensitivity/anaphylactic reaction, loss of consciousness, convulsion, parosmia, tachycardia, palpitation, dry mouth, malaise and feeling cold.

Adverse Reactions in Pediatric Patients

The frequency, type, and severity of adverse reactions observed in pediatric patients from the clinical studies were similar to adverse reactions in adults [see Use in Specific Populations (8.4)].

6.2 Postmarketing Experience

The following additional adverse reactions have been identified during postmarketing use of GADAVIST or other GBCAs. Because these reactions are reported voluntarily from a population of uncertain size, it is not possible to reliably estimate their frequency or establish a causal relationship to drug exposure.

Cardiac Disorders: Cardiac arrest

Gastrointestinal Disorders: Acute pancreatitis with onset within 48 hours after GBCA administration

General Disorders and Administration Site Conditions: Fatigue, asthenia, pain syndromes, and heterogeneous clusters of symptoms in the neurological, cutaneous, and musculoskeletal systems with variable onset and duration after GBCA administration [see Warnings and Precautions (5.5)]

Immune System Disorders: Hypersensitivity reactions (anaphylactic shock, circulatory collapse, respiratory arrest, bronchospasm, cyanosis, oropharyngeal swelling, laryngeal edema, blood pressure increased, chest pain, angioedema, conjunctivitis, hyperhidrosis, cough, sneezing, burning sensation, and pallor)

Renal Disorders: Nephrogenic systemic fibrosis

Respiratory, Thoracic, and Mediastinal Disorders: Acute respiratory distress syndrome, pulmonary edema

Skin Disorders: Gadolinium associated plaques

8 USE IN SPECIFIC POPULATIONS

8.1 Pregnancy

Risk Summary

GBCAs cross the placenta and result in fetal exposure. In human placental imaging studies, contrast was visualized in the placenta and fetal tissues after maternal GBCA administration. Based on animal studies, use of GBCAs during pregnancy may result in fetal gadolinium retention.

Published epidemiological studies on the association between GBCAs and adverse fetal outcomes have reported inconsistent findings and have important methodological limitations (see Data).

In animal reproduction studies, although teratogenicity was not observed, embryolethality was observed in monkeys, rabbits and rats receiving intravenous gadobutrol during organogenesis at doses 8 times and above the recommended human dose. Retardation of embryonal development was observed in rabbits and rats receiving intravenous gadobutrol during organogenesis at doses 8 and 12 times, respectively, the recommended human dose (see Data). Because of the potential risks of gadolinium to the fetus, use GADAVIST only if imaging is essential during pregnancy and cannot be delayed.

The background risk of major birth defects and miscarriage for the indicated population is unknown. All pregnancies have a background risk of birth defect, loss, or other adverse outcomes. In the U.S. general population, the estimated background risk of major birth defects and miscarriage in clinically recognized pregnancies is 2% to 4% and is 15% to 20%, respectively.

Data

Human Data

Available data regarding exposure to GBCAs during pregnancy from published epidemiological studies are not sufficient to assess the risk of adverse fetal and neonatal effects that may be associated with GBCAs. A retrospective cohort study of over 1.4 million pregnancies in Ontario, Canada, comparing pregnant women who had a GBCA MRI to pregnant women who did not have an MRI, reported a higher occurrence of stillbirths and neonatal deaths in the group receiving GBCA MRI. Limitations of this study include a lack of comparison with non-contrast MRI and lack of information about the maternal indication for MRI. Another retrospective cohort study of over 11 million pregnancies in the Medicaid database found no increased risk of fetal or neonatal death or Neonatal Intensive Care Unit admission when comparing pregnancies exposed to GBCA MRI versus non-contrast MRI. These two retrospective observational studies assessed a limited number of potential pregnancy outcomes and did not evaluate the full spectrum of potential fetal risk.

Animal Data

Gadolinium Retention

GBCAs administered to pregnant non-human primates (0.1 mmol/kg on gestational days 85 and 135) result in measurable gadolinium concentration in the offspring in bone, brain, skin, liver, kidney, and spleen for at least 7 months. GBCAs administered to pregnant mice (2 mmol/kg daily on gestational days 16 through 19) result in measurable gadolinium concentrations in the pups in bone, brain, kidney, liver, blood, muscle, and spleen at one month postnatal age.

Reproductive Toxicology

Embryolethality was observed when gadobutrol was administered intravenously to monkeys during organogenesis at doses 8 times the recommended single human dose (based on body surface area); gadobutrol was not maternally toxic or teratogenic at this dose. Embryolethality and retardation of embryonal development also occurred in pregnant rats receiving maternally toxic doses of gadobutrol (≥ 7.5 mmol/kg body weight; equivalent to 12 times the human dose based on body surface area) and in pregnant rabbits (≥ 2.5 mmol/kg body weight; equivalent to 8 times the recommended human dose based on body surface area). In rabbits, this finding occurred without evidence of pronounced maternal toxicity and with minimal placental transfer (0.01% of the administered dose detected in the fetuses). Because pregnant animals received repeated daily doses of GADAVIST, their overall exposure was significantly higher than that achieved with the standard single dose administered to humans.

8.2 Lactation

Risk Summary

There are no data on the presence of gadobutrol in human milk, the effects on the breastfed infant, or the effects on milk production. However, published lactation data on other GBCAs indicate that 0.01 to 0.04% of the maternal gadolinium dose is present in breast milk and there is limited GBCA gastrointestinal absorption in the breast-fed infant. Gadobutrol is present in rat milk (see Data). The developmental and health benefits of breastfeeding should be considered along with the mother's clinical need for GADAVIST and any potential adverse effects on the breastfed infant from GADAVIST or from the underlying maternal condition.

Data

In lactating rats receiving 0.5 mmol/kg of intravenous [^153Gd]-gadobutrol, 0.01% of the total administered radioactivity was transferred to the pup via maternal milk within 3 hours after administration, and the gastrointestinal absorption is poor (approximately 5% of the dose orally administered was excreted in the urine).

8.4 Pediatric Use

The safety and effectiveness of GADAVIST have been established in pediatric patients, including term neonates, for use with MRI to detect and visualize areas with disrupted blood brain barrier and/or abnormal vascularity of the CNS and for use in MRA to evaluate known or suspected supra-aortic or renal artery disease. Use of GADAVIST for these indications is supported by adequate and well-controlled studies in adults and by additional imaging, pharmacokinetic, and safety data from two studies (i.e., Trials 1 and 2) in a total of 182 pediatric patients aged less than 18 years, including term neonates, with CNS and non-CNS lesions. Trial 1 included 138 patients aged 2 to less than 18 years and Trial 2 included 44 patients aged less than 2 years [see Adverse Reactions (6.1), Clinical Pharmacology (12.3), and Clinical Studies (14.1, 14.3)].

The safety and effectiveness of GADAVIST have not been established in preterm neonates for any indication or in pediatric patients of any age for use with MRI to assess the presence and extent of malignant breast disease, or for use in CMRI to assess myocardial perfusion (stress, rest) and late gadolinium enhancement in patients with known or suspected coronary artery disease (CAD).

8.5 Geriatric Use

In clinical studies of GADAVIST, 1,377 patients were 65 years of age and over, while 104 patients were 80 years of age and over. No overall differences in safety or effectiveness were observed between these subjects and younger subjects, and other reported clinical experience has not identified differences between the elderly and younger patients.

This drug is known to be excreted by the kidney, and the risk of adverse reactions to this drug may be greater in patients with impaired renal function. Because elderly patients are more likely to have decreased renal function, it may be useful to monitor renal function [see Warnings and Precautions (5.2) and Use in Specific Populations (8.6)].

8.6 Renal Impairment

In patients with renal impairment, the exposure of gadobutrol is increased compared to patients with normal renal function. This may increase the risk of adverse reactions such as NSF. Prior to administration of GADAVIST, screen all patients for renal dysfunction by obtaining a history and/or laboratory tests. For patients receiving hemodialysis, consider the prompt initiation of hemodialysis following the administration of GADAVIST in order to enhance elimination of gadobutrol [see Warnings and Precautions (5.2) and Clinical Pharmacology (12.3)].

10 OVERDOSAGE

In the event of an overdose with GADAVIST, the substance can be removed by hemodialysis [see Clinical Pharmacology (12.3)].

For additional overdose management recommendations, consider contacting the Poison Help line at 1-800-222-1222 or consulting a medical toxicologist.

11 DESCRIPTION

GADAVIST (gadobutrol) injection is a paramagnetic macrocyclic gadolinium-based contrast agent for intravenous use.

The chemical name for gadobutrol is 10–[(1SR,2RS)–2,3–dihydroxy–1–hydroxymethylpropyl]–1,4,7,10–tetraazacyclododecane–1,4,7–triacetic acid, gadolinium complex. Gadobutrol is a water-soluble, hydrophilic compound with a partition coefficient between n-butanol and buffer at pH 7.6 of 0.006, and has a molecular formula of C18H31GdN4O9 and a molecular weight of 604.72. The structural formula of gadobutrol is:

GADAVIST is a sterile, clear, colorless to pale yellow solution. Each mL contains 604.72 mg (1 mmol) of gadobutrol (containing 1 mmol of gadolinium) and the following inactive ingredients: 0.513 mg of calcobutrol sodium, 1.211 mg of trometamol, hydrochloric acid (for pH adjustment), and water for injection. GADAVIST contains no preservatives.

The main physicochemical properties of GADAVIST are listed in Table 3.

Table 3: Physicochemical Properties of GADAVIST
Parameter | Value
Density (g/mL at 37°C) | 1.3
Osmolarity at 37°C (mOsm/L solution) | 1117
Osmolality at 37°C (mOsm/kg H2O) | 1603
Viscosity at 37°C (mPa∙s) | 4.96
pH | 6.6 to 8

The thermodynamic stability constants for gadobutrol (log Ktherm and log Kcond at pH 7.4) are 21.8 and 15.3, respectively.

12 CLINICAL PHARMACOLOGY

12.1 Mechanism of Action

Gadobutrol is a paramagnetic molecule (macrocyclic non-ionic complex of gadolinium) that develops a magnetic moment when placed in a magnetic field. The magnetic moment alters the relaxation rates of water protons in its vicinity in the body, leading to an increase in signal intensity (brightness) of tissues.

12.2 Pharmacodynamics

In MRI, visualization of normal and pathological tissue depends in part on variations in the radiofrequency signal intensity that occurs with:

- Differences in proton density
- Differences of the spin-lattice or longitudinal relaxation times (T1)
- Differences in the spin-spin or transverse relaxation time (T2)

When placed in a magnetic field, gadobutrol shortens the T1 and T2 relaxation times in targeted tissues. The extent to which a contrast agent can affect the relaxation rate of tissue water (1/T1 or 1/T2) is termed relaxivity (r1 or r2). The relaxivity of GBCAs is presented in Table 4.

Table 4: Relaxivity (r1) of GBCAs in Human Plasma at 1.5 T and 37°C
Gadolinium-Chelate | r1 (L∙mmol ^-1 ∙s^-1)
Gadobenate | 6.3
Gadobutrol | 5.2
Gadodiamide | 4.3
Gadopiclenol | 12.8
Gadoterate | 3.6
Gadoteridol | 4.1
Gadoxetate | 6.9

Compared to 0.5 molar gadolinium-based contrast agents, the higher concentration of GADAVIST results in half the volume of administration and a more compact contrast bolus injection. At the site of imaging, the relative height and width of the time intensity curve for GADAVIST varies as a function of imaging location and multiple patient, injection, and device-specific factors.

12.3 Pharmacokinetics

After intravenous administration of 0.1 mmol/kg GADAVIST, average plasma levels of gadobutrol are 0.59 mmol/L at 2 minutes after injection and 0.3 mmol/L at 60 minutes after injection, with an AUC of 1,072 µmol∙h/L. Values for further PK parameters are given in Table 5 below.

Distribution

After intravenous administration, gadobutrol is distributed in the extracellular space. Gadobutrol does not display any particular protein binding. Following GBCA administration, gadolinium is present for months or years in brain, bone, skin, and other organs [see Warnings and Precautions (5.5)].

Elimination

The average elimination half-life (t1/2) of gadobutrol is 1.8 hours.

Metabolism

Gadobutrol is not metabolized.

Excretion

Gadobutrol is excreted in an unchanged form through the kidneys by glomerular filtration. In healthy subjects, renal clearance of gadobutrol is 1.1 to 1.7 mL/(min∙kg) and thus comparable to the renal clearance of inulin.

Within 2 hours after intravenous administration more than 50% and within 12 hours more than 90% of the given dose is eliminated via the urine. Extra-renal elimination is negligible.

Specific Populations

Geriatric Patients

A single intravenous dose of 0.1 mmol/kg GADAVIST was administered to 15 elderly and 16 non-elderly subjects. AUC was slightly higher (43%) and clearance slightly lower (31%) in elderly subjects as compared to non-elderly subjects [see Use in Specific Populations (8.5)].

Pediatric Patients

The pharmacokinetics of gadobutrol were evaluated in a total of 173 pediatric patients aged less than 18 years (including term neonates) who received a single intravenous dose of 0.1 mmol/kg of GADAVIST. Table 5 shows the pharmacokinetic parameters of gadobutrol by age group. The pharmacokinetic profile of gadobutrol in pediatric patients is similar to that in adults, resulting in similar values for AUC, body weight normalized plasma clearance, as well as elimination half-life. Approximately 99% (median value) of the dose was recovered in urine within 6 hours (this information was derived from the 2 to less than 18 year-old age group).

Table 5: Pharmacokinetics by Age Group (Median [Range])
 | 0 to < 2 years N=43 | 2 to 6 years N=45 | 7 to 11 years N=39 | 12 to < 18 years N=46 | Adults N=93
AUC (µmol∙h/L) | 781 [513, 1891] | 846 [412, 1331] | 1025 [623, 2285] | 1237 [946, 2211] | 1072 [667, 1992]
CL (L/h/kg) | 0.128 [0.053, 0.195] | 0.119 [0.080, 0.215] | 0.099 [0.043, 0.165] | 0.081 [0.046, 0.103] | 0.094 [0.051, 0.150]
t1/2 (h) | 2.91 [1.60, 12.4] | 1.91 [1.04, 2.70] | 1.66 [0.91, 2.71] | 1.68 [1.31, 2.48] | 1.80 [1.20, 6.55]
C20 (µmol/L) | 367 [280, 427] | 421 [369, 673] | 462 [392, 760] | 511 [387, 1077] | 441 [281, 829]

Male and Female Patients

Gender has no clinically relevant effect on the pharmacokinetics of gadobutrol.

Patients with Renal Impairment

In patients with renal impairment, the serum half-life of gadobutrol is prolonged and correlated with the reduction in creatinine clearance.

After intravenous injection of GADAVIST 0.1 mmol/kg, the elimination half-life was 5.8 ± 2.4 hours in patients with mild to moderate renal impairment (80 > CLCR > 30 mL/min) and 17.6 ± 6.2 hours in patients with severe renal impairment not on dialysis (CLCR < 30 mL/min). The average AUC of gadobutrol in patients with normal renal function was 1.1 ± 0.1 mmol∙h/L, compared to 4.0 ± 1.8 mmol∙h/L in patients with mild to moderate renal impairment and 11.5 ± 4.3 mmol∙h/L in patients with severe renal impairment.

Complete recovery in the urine was seen in patients with mild or moderate renal impairment within 72 hours. In patients with severely impaired renal function about 80% of the administered dose was recovered in the urine within 5 days.

For patients receiving hemodialysis, 68% of gadobutrol is removed from the body after the first dialysis, 94% after the second dialysis, and 98% after the third dialysis session [see Warnings and Precautions (5.2) and Use in Specific Populations (8.6)].

13 NONCLINICAL TOXICOLOGY

13.1 Carcinogenesis, Mutagenesis, Impairment of Fertility

Carcinogenesis

No carcinogenicity studies of gadobutrol have been conducted.

Mutagenesis

Gadobutrol was not mutagenic in in vitro reverse mutation tests in bacteria, in the HGPRT (hypoxanthine-guanine phosphoribosyl transferase) test using cultured Chinese hamster V79 cells, or in chromosome aberration tests in human peripheral blood lymphocytes, and was negative in an in vivo micronucleus test in mice after intravenous injection of 0.5 mmol/kg.

Impairment of Fertility

Gadobutrol had no effect on fertility and general reproductive performance of male and female rats when given in doses 12.2 times the human equivalent dose (based on body surface area).

13.2 Animal Toxicology and/or Pharmacology

Local intolerance reactions, including moderate irritation associated with infiltration of inflammatory cells was observed after paravenous administration to rabbits, suggesting the possibility of occurrence of local irritation if the contrast medium leaks around veins in a clinical setting [see Warnings and Precautions (5.7)].

14 CLINICAL STUDIES

14.1 MRI of the CNS

The effectiveness of GADAVIST for the visualization of lesions was evaluated in two clinical trials (i.e., Studies 1 and 2) in patients who were referred for MRI of the CNS with contrast. In both studies, patients underwent a baseline, pre-contrast MRI prior to administration of GADAVIST at a dose of 0.1 mmol/kg, followed by a post-contrast MRI. In Study 1, patients also underwent an MRI before and after the administration of gadoteridol. The studies were designed to demonstrate superiority of GADAVIST MRI to non-contrast MRI for lesion visualization. For both studies, pre-contrast and pre-plus-post contrast images (paired images) were independently evaluated by three readers for contrast enhancement and border delineation using a scale of 1 to 4, and for internal morphology using a scale of 1 to 3 (Table 6). Lesion counting was also performed to demonstrate non-inferiority of paired GADAVIST image sets to pre-contrast MRI. Readers were blinded to clinical information.

Table 6: Primary Endpoint Visualization Scoring System
Score | Visualization Characteristics
Score | Contrast Enhancement | Border Delineation | Internal Morphology
1 | None | None | Poorly visible
2 | Weak | Moderate | Moderately visible
3 | Clear | Clear but incomplete | Sufficiently visible
4 | Clear and bright | Clear and complete | N/A

A total of 657 patients were evaluated. The average age was 49 years (range 18 to 85 years) and 42% were male. The racial and ethnic representations were 39% White, 4% Black or African American, 16% Hispanic or Latino, 38% Asian, and 3% of other ethnic groups.

Table 7 shows a comparison of visualization results between paired images and pre-contrast images. GADAVIST provided a statistically significant improvement for each of the three lesion visualization parameters when averaged across three independent readers for each study.

Table 7: Visualization Endpoint Results of Central Nervous System Adult MRI Studies with 0.1 mmol/kg GADAVIST
Endpoint | Study 1 N=336 |  |  | Study 2 N=321
Endpoint | Pre-contrast | Paired | Difference [Difference of means = (paired mean) – (pre-contrast mean)] | Pre-contrast | Paired | Difference
Contrast Enhancement | 0.97 | 2.26 | 1.29 [p<0.001] | 0.93 | 2.86 | 1.94
Border Delineation | 1.98 | 2.58 | 0.60 | 1.92 | 2.94 | 1.02
Internal Morphology | 1.32 | 1.93 | 0.60 | 1.57 | 2.35 | 0.78
Average # Lesions Detected | 8.08 | 8.25 | 0.17 [Did not meet noninferiority margin of -0.35] | 2.65 | 2.97 | 0.32 [Met noninferiority margin of -0.35]

Performances of GADAVIST and gadoteridol for visualization parameters were similar. Regarding the number of lesions detected, Study 2 met the prespecified noninferiority margin of -0.35 for paired read versus pre-contrast read while in Study 1, GADAVIST and gadoteridol did not.

For the visualization endpoints contrast enhancement, border delineation, and internal morphology, the percentage of patients scoring higher for paired images compared to pre-contrast images ranged from 93% to 99% for Study 1, and 95% to 97% for Study 2. For both studies, the mean number of lesions detected on paired images exceeded that of the pre-contrast images; 37% for Study 1 and 24% for Study 2. There were 29% and 11% of patients in which the pre-contrast images detected more lesions for Study 1 and Study 2, respectively.

The percentage of patients whose average reader mean score changed by ≤ 0, up to 1, up to 2, and ≥ 2 scoring categories presented in Table 6 is shown in Table 8. The categorical improvement of (≤ 0) represents higher (< 0) or identical (= 0) scores for the pre-contrast read, the categories with scores > 0 represent the magnitude of improvement seen for the paired read.

Table 8: Primary Endpoint Visualization Categorical Improvement for Average Reader
 | Study 1 N=336 |  |  |  | Study 2 N=321
Endpoint | Categorical Improvement (Paired – Pre-Contrast) % |  |  |  | Categorical Improvement (Paired – Pre-Contrast) %
 | ≤ 0 | > 0 – < 1 | 1 – < 2 | ≥ 2 | ≤ 0 | > 0 – < 1 | 1 – < 2 | ≥ 2
Contrast Enhancement | 1 | 30 | 55 | 13 | 3 | 6 | 34 | 57
Border Delineation | 7 | 73 | 18 | 1 | 5 | 38 | 51 | 5
Internal Morphology | 4 | 79 | 17 | 0 | 5 | 61 | 33 | 1

For both studies, the improvement of visualization endpoints in paired GADAVIST images compared to pre-contrast images resulted in improved assessment of normal and abnormal CNS anatomy.

14.2 MRI of the Breast

The effectiveness of GADAVIST for the ability to assess the presence and extent of malignant breast disease was evaluated in two identical clinical trials (i.e., Studies 3 and 4) in patients with recently diagnosed breast cancer prior to surgery. Patients underwent non-contrast breast MRI (BMR) prior to GADAVIST (0.1 mmol/kg) breast MRI. BMR images and GADAVIST BMR (combined contrast plus non-contrast) images were independently evaluated in each study by three readers blinded to clinical information. In separate reading sessions the BMR images and GADAVIST BMR images were also interpreted together with X-ray mammography images (XRM).

A total of 787 patients were evaluated: Study 3 enrolled 390 female patients with an average age of 56 years and racial distribution of 74% White, 25% Asian, 0.5% Black or African American, and 0.5% other; Study 4 enrolled 396 female patients and 1 male patient with an average age of 57 years and racial distribution of 71% White, 24% Asian, 3% Black or African American, and 2% other.

The readers assessed 5 regions per breast for the presence of malignancy using each reading modality. The readings were compared to an independent standard of truth (SoT) consisting of histopathology for all regions where excisions were made and tissue evaluated. XRM plus ultrasound was used for all other regions.

The assessment of malignant disease was performed using a region based within-subject sensitivity. Sensitivity for each reading modality was defined as the mean of the percentage of malignant breast regions correctly interpreted for each subject. The within-subject sensitivity of GADAVIST BMR was superior to that of BMR. The lower bound of the 95% Confidence Interval (CI) for the difference in within-subject sensitivity ranged from 19% to 42% for Study 3 and from 12% to 27% for Study 4. The within-subject sensitivity for GADAVIST BMR and BMR as well as for GADAVIST BMR plus XRM and BMR plus XRM is presented in Table 9.

Table 9: Sensitivity of GADAVIST BMR for Detection of Malignant Breast Disease
Study 3 |  |  |  |  | Study 4
Sensitivity (%) N=388 Patients |  |  |  |  | Sensitivity (%) N=390 Patients
Reader | BMR | BMR + XRM | GADAVIST BMR | GADAVIST BMR +XRM | Reader | BMR | BMR + XRM | GADAVIST BMR | GADAVIST BMR +XRM
1 | 37 | 71 | 83 | 84 | 4 | 73 | 83 | 87 | 90
2 | 49 | 76 | 80 | 83 | 5 | 57 | 81 | 89 | 90
3 | 63 | 75 | 87 | 87 | 6 | 55 | 80 | 86 | 88

Specificity was defined as the percentage of non-malignant breasts correctly identified as non-malignant. The lower limit of the 95% confidence interval for specificity of GADAVIST BMR was greater than 80% for 5 of 6 readers. (Table 10)

Table 10: Specificity of GADAVIST BMR in Non-Malignant Breasts
Study 3 |  |  | Study 4
Specificity (%) N=372 Patients |  |  | Specificity (%) N=367 Patients
Reader | GADAVIST BMR | Lower Limit 95% CI | Reader | GADAVIST BMR | Lower Limit 95% CI
1 | 86 | 82 | 4 | 92 | 89
2 | 95 | 93 | 5 | 84 | 80
3 | 89 | 85 | 6 | 83 | 79

Three additional readers in each study read XRM alone. For these readers over both studies, sensitivity ranged from 68% to 73% and specificity in non-malignant breasts ranged from 86% to 94%.

In breasts with malignancy, a false positive detection rate was calculated as the percentage of subjects for which the readers assessed a region as malignant which could not be verified by SoT. The false positive detection rates for GADAVIST BMR ranged from 39% to 53% (95% CI Upper Bounds ranged from 44% to 58%).

14.3 MRA

The effectiveness of GADAVIST for the ability to evaluate known or suspected supra-aortic or renal artery disease was evaluated in two clinical trials (i.e., Studies 5 and 6). Study 5 enrolled patients with known or suspected disease of the supra-aortic arteries (for evaluation up to but excluding the basilar artery), and Study 6 enrolled patients with known or suspected disease of the renal arteries. In both studies, non-contrast, 2D time-of-flight (ToF) magnetic resonance angiography (MRA) was performed prior to GADAVIST MRA using a single intravenous injection of 0.1 mmol/kg. The injection rate of 1.5 mL/second was selected to extend the injection duration to at least half of the imaging duration. Imaging was performed with parallel-channel, 1.5T MRI devices and an automatic bolus tracking technique to trigger the image acquisition following GADAVIST administration using elliptically encoded, T1-weighted, 3D gradient-echo image acquisition and single breath hold. Three central readers blinded to clinical information interpreted the ToF and GADAVIST MRA images. Three additional central readers interpreted separately acquired computed tomographic angiography (CTA) images, which were used as the standard of reference (SoR) in each study.

A total of 749 patients were evaluated. The 457 patients in Study 5 had an average age of 68 years (range 25 to 93 years) and were 64% male with a racial distribution of 80% White, 28% Black or African American, and 16% Asian. The 292 patients in Study 6 had an average age of 55 years (range 18 to 88 years) and were 54% male with a racial distribution of 68% White, 7% Black or African American, and 22% Asian.

Efficacy was evaluated based on anatomical visualization and performance for distinguishing between normal and abnormal anatomy. The visualization metric depended on whether readers selected, "Yes, it can be visualized along its entire length..." when responding to the question, "Is this segment assessable?" Twenty-one segments in Study 5 and six segments in Study 6 were presented per subject to each reader. The performance metrics, sensitivity and specificity, depended on digital caliper-based quantitation of arterial narrowing in visualized, non-occluded, abnormal-appearing segments. Significant stenosis was defined as at least 70% in Study 5 and 50% in Study 6. Performance of GADAVIST MRA compared to ToF MRA was calculated using an imputation method for non-visualized segments by assigning them as a 50% match with SoR and a 50% mismatch. Performance of GADAVIST MRA compared to a pre-specified threshold of 50% was calculated after excluding non-visualized segments. Measurement variability and visualization of accessory renal arteries was also evaluated.

Results were analyzed for each of the three central readers.

Table 11: Visualization, Sensitivity, Specificity
STUDY 5: SUPRA-AORTIC ARTERIES (457 patients)
Performance at the segment level
9597 [Number of segments varied between readers; number for majority-reader shown.] segments of which 158 were positive for stenosis by SoR [Standard of Reference based on aggregate interpretation of three central CTA readers.]
 | VISUALIZATION (%) |  |  | SENSITIVITY (%) |  |  | SPECIFICITY (%)
READER | GAD MRA | ToF MRA | GAD − ToF (CI [95.1/95% (Study 5/6) confidence interval for two-sided comparison.]) | GAD MRA | ToF MRA | GAD − ToF (CI [90.1/90% (Study 5/6) confidence interval for one-sided comparison against non-inferiority margin of -7.5.]) | GAD MRA | ToF MRA | GAD − ToF (CI)
1 | 88 | 24 | 64 (61, 67) | 60 | 54 | 6 (-4, 14) | 92 | 62 | 30 (29, 32)
2 | 95 | 75 | 20 (18, 21) | 60 | 54 | 6 (-3, 14) | 95 | 85 | 10 (9, 11)
3 | 97 | 82 | 15 (13, 17) | 58 | 55 | 3 (-4, 11) | 97 | 89 | 8 (7, 9)
STUDY 6: RENAL ARTERIES (292 patients)
Performance at the segment level
1752 segments of which 133 were positive for stenosis by SoR
4 | 98 | 82 | 16 (13, 20) | 52 | 51 | 1 (-9, 11) | 94 | 83 | 11 (9, 14)
5 | 96 | 72 | 24 (21, 28) | 54 | 39 | 15 (6, 24) | 95 | 85 | 10 (8, 12)
6 | 96 | 78 | 17 (14, 21) | 53 | 50 | 3 (-6, 12) | 94 | 81 | 13 (11, 16)

GAD MRA = Post-contrast GADAVIST Magnetic Resonance Angiography, ToF = Non-contrast 2D-Time of Flight.

For all three supra-aortic artery readers in Study 5, the lower bound of confidence for the sensitivity of GADAVIST MRA did not exceed 54%. For all three renal artery readers in Study 6, the lower bound of confidence for the sensitivity of GADAVIST MRA did not exceed 46%.

Measurement Variability

For both MRA and CTA, readers varied in the quantity of narrowing they assigned to the same arterial segments. Table 12 shows the percentage of patients in whom the measurement range was 30% or greater for the left or right internal carotid and proximal renal artery segments. There were approximately four measurements per patient segment, one from the site and three central readers. Measurement variability was high for both CTA and MRA, but numerically lower for GADAVIST compared to non-contrast ToF MRA.

Table 12: Percent of Patients with Range ≥ 30%, ≥ 50%, ≥ 70% for Measurement of Stenoses and Normal Vessel Diameters
 | Internal Carotid |  |  |  | Proximal Main Renal
 | N | ≥ 30% | ≥ 50% | ≥ 70% | N | ≥ 30% | ≥ 50% | ≥ 70%
CTA | 456 | 40 | 11 | 4 | 292 | 59 | 33 | 9
ToF MRA | 443 | 55 | 22 | 9 | 270 | 44 | 22 | 9
GADAVIST MRA | 454 | 47 | 13 | 4 | 286 | 34 | 14 | 4

Visualization of Accessory Renal Arteries for Surgical Planning and Renal Donor Evaluation (Study 6 only)

Of 1,752 main arteries visualized by the central CTA readers, 266 (15%) were also associated with positive visualization of at least one accessory (duplicate) artery. With the central MRA readers, the comparable rates were 232 of 1752 (13%) for GADAVIST MRA compared to 53 of 1,752 (3%) for ToF MRA.

14.4 Cardiac MRI

The effectiveness of GADAVIST for detection of coronary artery disease (CAD) was evaluated in two multi-center, open-label clinical trials (i.e., Studies 7 and 8) in adult patients with known or suspected CAD. Patients were excluded from study if they had a history of coronary artery bypass grafting, or if it was known in advance that they were unable to hold their breath, or had atrial fibrillation or other arrhythmia likely to prevent electrocardiogram-gated CMRI.

A total of 764 patients were evaluated. The 376 patients in Study 7 had an average age of 59 years (range 20 to 84 years) and were 69% male with a racial distribution of 74% White, 1% Black or African American, and 25% Asian. The 388 patients in Study 8 had an average age of 59 years (range 23 to 82 years) and were 61% male with a racial distribution of 67% White, 17% Black or African American, and 12% Asian.

All subjects underwent dynamic first-pass GADAVIST imaging during vasodilator stress, followed ~10 minutes later by dynamic first-pass GADAVIST imaging at rest, followed ~5 minutes later with imaging during a period of gradual GADAVIST washout from the myocardium (late gadolinium enhancement, LGE). Imaging was performed on 1.5 T or 3.0 T MRI devices equipped with multichannel surface coils to support accelerated acquisitions with parallel imaging, T1-weighted, 2D gradient-echo, dynamic acquisition of perfusion with at least 3 slices per heartbeat. GADAVIST was administered intravenously at a rate of ~4 mL/second as two separate bolus injections (0.05 mmol/kg each), the first at peak pharmacologic stress (~3 minutes after start of ongoing adenosine infusion, or immediately after completion of regadenoson administration, at approved doses). No additional GADAVIST was administered for LGE imaging.

Images were read by three independent readers blinded to clinical information. Reader detection of CAD depended on visually detecting defective perfusion or scar on GADAVIST CMRI (stress, rest, LGE) imaging. Quantitative coronary angiography (QCA) was used to measure intraluminal narrowing and served as the standard of reference (SoR). Computed tomographic angiography (CTA) was used as the SoR if disease could be unequivocally excluded, and no coronary angiography (CA) was available. The left ventricular myocardium was divided into six regions. Readers provided per-region (CMRI, CTA) and per-artery (QCA) interpretations for each subject. Subject-level endpoints reflected each subject's most abnormal localized finding.

The sensitivity results for GADAVIST CMRI to detect CAD defined as either maximum stenosis ≥ 50% or ≥ 70% by QCA are presented in Table 13. For each reader, sensitivity of GADAVIST CMRI larger than 60% can be concluded if the lower 95% confidence limit of the sensitivity estimate exceeds the pre-specified threshold of 60%.

Table 13: Sensitivity (%) of GADAVIST-CMRI for Detection of CAD in Patients with Maximum Stenosis [Stenosis determined by Quantitative Coronary Angiography (QCA)] of ≥ 50% and ≥ 70%
 | Study 7 |  | Study 8
 | ≥ 50% N=141 | ≥ 70% N=108 | ≥ 50% N=150 | ≥ 70% N=105
Reader 1 [CMRI images were assessed by six independent blinded readers, three in each study.] | 77 (69, 83) [The bolded value represents the lower limit of the 95% confidence interval, which is compared to a pre-specified threshold of 60% for evaluation of sensitivity.] | 90 (83, 95) | 65 (57, 72) | 77 (68, 85)
Reader 2 | 65 (57, 73) | 80 (71, 87) | 56 (48, 64) | 71 (62, 80)
Reader 3 | 65 (56, 72) | 79 (70, 86) | 61 (53, 69) | 76 (67, 84)

The specificity results for GADAVIST CMRI to detect CAD defined as either maximum stenosis ≥ 50% or ≥ 70% by QCA are presented in Table 14. For each reader, specificity of GADAVIST CMRI larger than 55% can be concluded if the lower 95% confidence limit of the specificity estimate exceeds the pre-specified threshold of 55%.

Table 14: Specificity (%) of GADAVIST CMRI for Exclusion of CAD in Patients with Maximum Stenosis [Stenosis determined by Quantitative Coronary Angiography (QCA)] of ≥ 50% and ≥ 70%
 | Study 7 |  | Study 8
 | ≥ 50% N=235 | ≥ 70% N=268 | ≥ 50% N=239 | ≥ 70% N=283
Reader 1 [CMRI images were assessed by six independent blinded readers, three in each study.] | 85 (80, 89) [The bolded value represents the lower limit of the 95% confidence interval, which is compared to a pre-specified threshold of 55% for evaluation of specificity.] | 83 (78, 87) | 85 (80, 90) | 82 (77, 86)
Reader 2 | 92 (88, 95) | 91 (87, 94) | 89 (84, 92) | 87 (83, 91)
Reader 3 | 92 (88, 95) | 91 (87, 94) | 90 (85, 93) | 87 (82, 91)

In Study 7, among the 33 patients with maximum stenosis by QCA between 50% and <70%, the proportion of GADAVIST-CMRI positive detections of CAD ranged from 15% to 33%. In Study 8, among the 45 patients with maximum stenosis by QCA between 50% and < 70%, the proportion of GADAVIST-CMRI positive detections of CAD ranged from 20% to 35%. The results of GADAVIST-CMRI reads to detect CAD in patients with maximum stenosis between 50% and < 70% are summarized in Table 15.

Table 15: GADAVIST-CMRI Detection of CAD in Patients with Maximum Stenosis [Stenosis determined by Quantitative Coronary Angiography (QCA).] between 50% and < 70%
 | Study 7 (n=33) | Study 8 (n=45)
 | GADAVIST-CMRI positive | GADAVIST-CMRI positive
Reader 1 [CMRI images were assessed by six independent blinded readers, three in each study.] | 11 (33%) | 16 (35%)
Reader 2 | 5 (15%) | 9 (20%)
Reader 3 | 6 (18%) | 12 (26%)

Left Mainstem Stenosis

The studies did not include sufficient numbers of subjects to characterize the performance of GADAVIST CMRI for detection of left mainstem stenosis (LMS), a subgroup at high risk from false negative reads. In Studies E and F, only three subjects had isolated LMS stenosis >50%. In two of the three cases, the CMRI was interpreted as normal by at least two of the three readers (false negative). Sixteen subjects had LMS stenosis >50% (including subjects with isolated LMS stenosis and subjects with LMS stenosis in addition to stenoses elsewhere). In five of these sixteen cases, the CMR was interpreted as normal by at least two of the three readers (false negative).

16 HOW SUPPLIED/STORAGE AND HANDLING

How Supplied

GADAVIST (gadobutrol) injection is supplied at a concentration of 1 mmol/mL of gadobutrol as a clear and colorless to pale yellow solution available in the following strengths:

Strength | Package Type | Sale Unit | NDC
2 mmol/2 mL (1 mmol/mL) | Single-Dose Vial | Boxes of 5 cartons containing 3 vials each (15 total) | 50419-325-37
7.5 mmol/7.5 mL (1 mmol/mL) | Single-Dose Vial | Boxes of 2 cartons containing 10 vials each (20 total) | 50419-325-11
10 mmol/10 mL (1 mmol/mL) | Single-Dose Vial | Boxes of 2 cartons containing 10 vials each (20 total) | 50419-325-12
15 mmol/15 mL (1 mmol/mL) | Single-Dose Vial | Boxes of 2 cartons containing 10 vials each (20 total) | 50419-325-13
7.5 mmol/7.5 mL (1 mmol/mL) | Single-Dose Prefilled Syringe | Boxes of 5 syringes | 50419-325-27
10 mmol/10 mL (1 mmol/mL) | Single-Dose Prefilled Syringe | Boxes of 5 syringes | 50419-325-28
15 mmol/15 mL (1 mmol/mL) | Single-Dose Prefilled Syringe | Boxes of 5 syringes | 50419-325-29
30 mmol/30 mL (1 mmol/mL) | Imaging Bulk Package | Boxes of 2 cartons containing 5 bottles each (10 total) | 50419-325-18
65 mmol/65 mL (1 mmol/mL) | Imaging Bulk Package | Boxes of 10 bottles | 50419-325-19

Storage and Handling

Store at 25°C (77°F); excursions permitted to 15°C to 30°C (59°F to 86°F) [see USP Controlled Room Temperature].

If solidification occurs due to cold exposure, bring GADAVIST to room temperature before use and inspect to ensure that the solution is clear and colorless to pale yellow.

17 PATIENT COUNSELING INFORMATION

Advise the patient to read the FDA-approved patient labeling (Medication Guide).

Nephrogenic Systemic Fibrosis

Inform the patient that GADAVIST may increase the risk of NSF among patients with impaired elimination of the drug and that NSF may result in fatal or debilitating fibrosis affecting the skin, muscle, and internal organs.

Instruct the patients to contact their physician if they develop signs or symptoms of NSF following GADAVIST administration, such as burning, itching, swelling, scaling, hardening and tightening of the skin; red or dark patches on the skin; stiffness in joints with trouble moving, bending or straightening the arms, hands, legs or feet; pain in the hip bones or ribs; or muscle weakness [see Warnings and Precautions (5.2)].

Acute Respiratory Distress Syndrome

Advise patients that acute respiratory distress syndrome (ARDS) has occurred with GADAVIST. Inform patients on the symptoms of the observed ARDS cases, and instruct patients to inform their healthcare provider if they experience these symptoms [see Warnings and Precautions (5.4)].

Gadolinium Retention

Advise patients that gadolinium is retained for months or years in brain, bone, skin, and other organs following GADAVIST administration even in patients with normal renal function. The clinical consequences of retention are unknown. Retention depends on multiple factors and is greater following administration of linear GBCAs than following administration of macrocyclic GBCAs [see Warnings and Precautions (5.5)].

Pregnancy

Advise pregnant women of the potential risk of fetal exposure to GADAVIST [see Use in Specific Populations (8.1)].

Manufactured for:
Bayer HealthCare Pharmaceuticals Inc.
Whippany, NJ 07981

Manufactured in Germany

© 2011, Bayer HealthCare Pharmaceuticals Inc. All rights reserved.

MEDICATION GUIDE
GADAVIST (gad-a-vist)
(gadobutrol)
Injection, for intravenous use

What is the most important information I should know about GADAVIST?

- GBCAs like GADAVIST may cause serious side effects including death, coma, encephalopathy, and seizures when it is given intrathecally (injection given into the spinal canal). It is not known if GADAVIST is safe and effective with intrathecal use. GADAVIST is not approved for this use.
- GADAVIST contains a metal called gadolinium. Small amounts of gadolinium can stay in your body including the brain, bones, skin and other parts of your body for a long time (several months to years).
- It is not known how gadolinium may affect you, but so far, studies have not found harmful effects in patients with normal kidneys.
- Rarely, patients have reported pains, tiredness, and skin, muscle or bone ailments for a long time, but these symptoms have not been directly linked to gadolinium.
- There are different GBCAs that can be used for your MRI exam. The amount of gadolinium that stays in the body is different for different gadolinium medicines. Gadolinium stays in the body more after gadodiamide than after gadoxetate disodium or gadobenate dimeglumine. Gadolinium stays in the body the least after gadoterate meglumine, gadobutrol, gadoteridol, and gadopiclenol.
- People who get many doses of gadolinium medicines, women who are pregnant and young children may be at increased risk from gadolinium staying in the body.
- Some people with kidney problems who get gadolinium medicines can develop a condition with severe thickening of the skin, muscles and other organs in the body (nephrogenic systemic fibrosis). Your healthcare provider should screen you to see how well your kidneys are working before you receive GADAVIST.

What is GADAVIST?

- GADAVIST is a prescription medicine called a gadolinium-based contrast agent (GBCA). GADAVIST, like other GBCAs, is injected into your vein and used with a magnetic resonance imaging (MRI) scanner.
- An MRI exam with a GBCA, including GADAVIST, helps your doctor to see problems better than an MRI exam without a GBCA.
- Your doctor has reviewed your medical records and has determined that you would benefit from using a GBCA with your MRI exam.

Do not receive GADAVIST if you have had a severe allergic reaction to GADAVIST.

Before receiving GADAVIST, tell your healthcare provider about all your medical conditions, including if you:

- have had any MRI procedures in the past where you received a GBCA. Your healthcare provider may ask you for more information including the dates of these MRI procedures.
- are pregnant or plan to become pregnant. It is not known if GADAVIST can harm your unborn baby. Talk to your healthcare provider about the possible risks to an unborn baby if a GBCA such as GADAVIST is received during pregnancy.
- have kidney problems, diabetes, or high blood pressure.
- have had an allergic reaction to dyes (contrast agents) including GBCAs.

What are the possible side effects of GADAVIST?

- See "What is the most important information I should know about GADAVIST?"
- Allergic reactions. GADAVIST can cause allergic reactions that can sometimes be serious. Your healthcare provider will monitor you closely for symptoms of an allergic reaction.
- A serious lung problem called acute respiratory distress syndrome (ARDS). Call your healthcare provider right away if you have shortness of breath with or without a fever, trouble breathing, or a fast rate of breathing after receiving GADAVIST.

The most common side effects of GADAVIST include: headache, nausea, and dizziness.
These are not all the possible side effects of GADAVIST.
Call your doctor for medical advice about side effects. You may report side effects to FDA at 1-800-FDA-1088.

General information about the safe and effective use of GADAVIST.
Medicines are sometimes prescribed for purposes other than those listed in a Medication Guide. You can ask your healthcare provider for information about GADAVIST that is written for health professionals.

What are the ingredients in GADAVIST?
Active ingredient: gadobutrol
Inactive ingredients: calcobutrol sodium, trometamol, hydrochloric acid (for pH adjustment) and water for injection
Manufactured for Bayer HealthCare Pharmaceuticals Inc.
Manufactured in Germany © 2011
Bayer HealthCare Pharmaceuticals Inc. All rights reserved.
For more information, go to www.gadavist.com or call 1-888-842-2937.

This Medication Guide has been approved by the U.S. Food and Drug Administration.

Revised: 2/2026

PACKAGE/LABEL PRINCIPAL DISPLAY PANEL

Gadavist Imaging Bulk Pack 65 mL Label

Dose: 0.1 mL/kg

NDC 50419-325-09
65 mL

Rx only

sterile solution

Gadavist

sterile solution

Gadavist

(gadobutrol) injection
1 mmol/mL

For Intravenous Administration.
Multiple-Dose container.

Discard unused portion 24 hours after initial puncture.